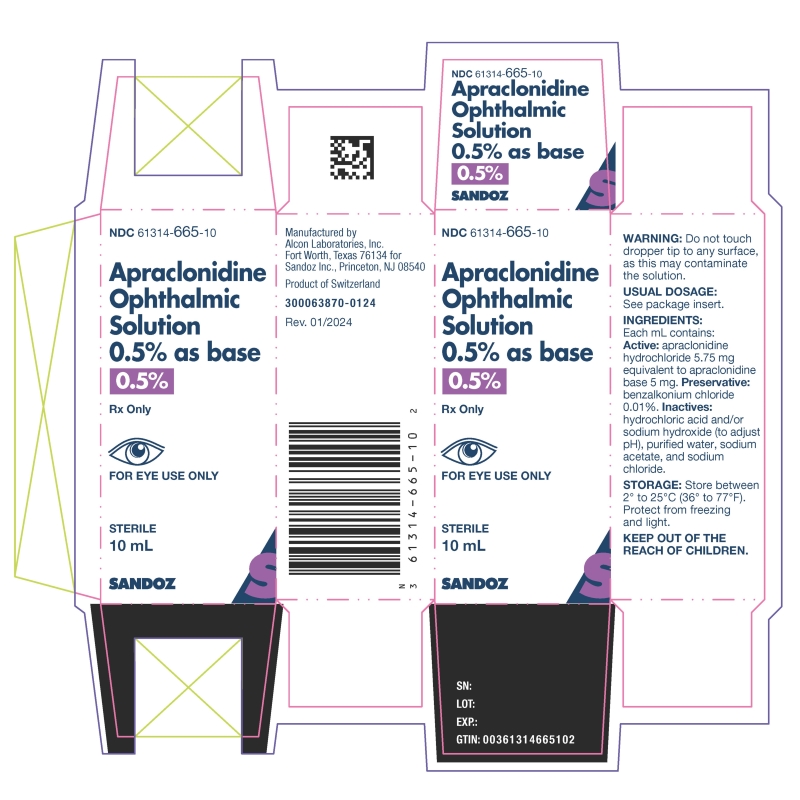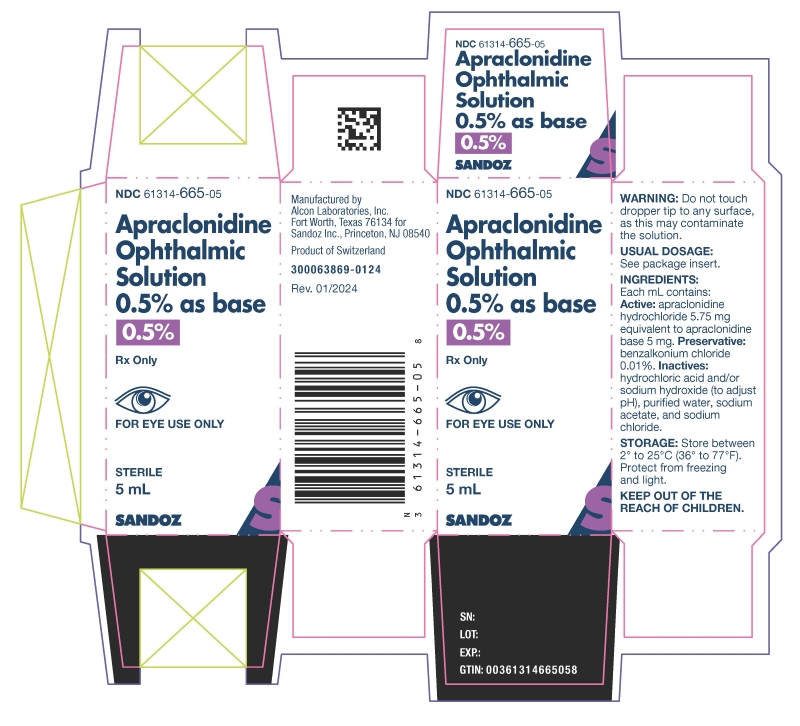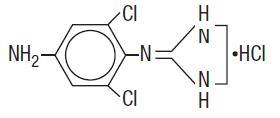 DRUG LABEL: Apraclonidine
NDC: 61314-665 | Form: SOLUTION
Manufacturer: Sandoz Inc
Category: prescription | Type: HUMAN PRESCRIPTION DRUG LABEL
Date: 20241002

ACTIVE INGREDIENTS: APRACLONIDINE HYDROCHLORIDE 5.75 mg/1 mL
INACTIVE INGREDIENTS: BENZALKONIUM CHLORIDE; SODIUM CHLORIDE; SODIUM ACETATE; SODIUM HYDROXIDE; HYDROCHLORIC ACID; WATER

Apraclonidine Ophthalmic Solution, 0.5% as base
Rx Only

DESCRIPTION

Apraclonidine ophthalmic solution 0.5% contains apraclonidine hydrochloride, an alpha adrenergic agonist, in a sterile isotonic solution for topical application to the eye. Apraclonidine hydrochloride is a white to off-white powder and is highly soluble in water. Its chemical name is 2-[(4-amino-2,6 dichlorophenyl) imino]imidazolidine monohydrochloride with an empirical formula of C9H11Cl3N4 and a molecular weight of 281.57 g/mol. The chemical structure of apraclonidine hydrochloride is:

Each mL of apraclonidine ophthalmic solution 0.5% contains: Active: apraclonidine hydrochloride 5.75 mg equivalent to apraclonidine base 5 mg. Preservative: benzalkonium chloride 0.01%. Inactives: hydrochloric acid and/or sodium hydroxide (to adjust pH), purified water, sodium acetate, and sodium chloride.

CLINICAL PHARMACOLOGY

Apraclonidine hydrochloride is a relatively selective alpha-2-adrenergic agonist. When instilled in the eye, apraclonidine ophthalmic solution 0.5%, has the action of reducing elevated, as well as normal, intraocular pressure (IOP), whether or not accompanied by glaucoma. Ophthalmic apraclonidine has minimal effect on cardiovascular parameters. Elevated IOP presents a major risk factor in glaucomatous field loss. The higher the level of IOP, the greater the likelihood of optic nerve damage and visual field loss. Apraclonidine ophthalmic solution 0.5% has the action of reducing IOP. The onset of action of apraclonidine can usually be noted within one hour, and maximum IOP reduction occurs about three hours after instillation. Aqueous fluorophotometry studies demonstrate that apraclonidine's predominant mechanism of action is reduction of aqueous flow via stimulation of the alpha-adrenergic system.

Repeated dose-response and comparative studies (0.125%-1.0% apraclonidine) demonstrate that 0.5% apraclonidine is at the top of the dose-response IOP reduction curve.

The clinical utility of apraclonidine ophthalmic solution 0.5% is most apparent for those glaucoma patients on maximally tolerated medical therapy. Patients on maximally tolerated medical therapy with uncontrolled IOP, and scheduled to undergo laser trabeculoplasty or trabeculectomy surgery were enrolled into a double-masked, placebo-controlled, multicenter clinical trial to determine if apraclonidine ophthalmic solution 0.5%, dosed three times daily, could delay the need for surgery for up to three months.

All patients enrolled into this trial had advanced glaucoma and were undergoing maximally tolerated medical therapy, i.e., patients were using combinations of a topical beta blocker, sympathomimetics, parasympathomimetics and oral carbonic anhydrase inhibitors. Patients were considered to be treatment failures in this study if, in the opinion of the investigators, their IOP was uncontrolled by the masked study medication or there was evidence of further optic nerve damage or visual field loss, and surgery was indicated. Of 171 patients receiving masked medication, 84 were treated with apraclonidine ophthalmic solution 0.5% and 87 were treated with placebo (apraclonidine vehicle).

Apraclonidine treatment resulted in a significantly greater percentage of treatment successes compared to patients treated with placebo. In this placebo-controlled maximum therapy trial, 14.3% of patients treated with apraclonidine ophthalmic solution 0.5% were discontinued due to adverse events, primarily allergic-like reactions (12.9%).

The IOP lowering efficacy of apraclonidine ophthalmic solution 0.5% diminishes over time in some patients. This loss of effect, or tachyphylaxis, appears to be an individual occurrence with a variable time of onset and should be closely monitored.

An unpredictable decrease of IOP control in some patients, incidence of ocular allergic responses and systemic side effects, may limit the utility of apraclonidine ophthalmic solution 0.5%. However, patients on maximally tolerated medical therapy may still benefit from the additional IOP reduction provided by the short-term use of apraclonidine ophthalmic solution 0.5%.

Topical use of apraclonidine ophthalmic solution 0.5% leads to systemic absorption. Studies of apraclonidine ophthalmic solution 0.5% dosed one drop three times a day in both eyes for 10 days, in normal volunteers, yielded mean peak and trough concentrations of 0.9 ng/mL and 0.5 ng/mL, respectively. The half-life of apraclonidine ophthalmic solution 0.5% was calculated to be 8 hours.

Apraclonidine ophthalmic solution 0.5%, because of its alpha adrenergic activity, is a vasoconstrictor. Single dose ocular blood flow studies in monkeys, using the microsphere technique, demonstrated a reduced blood flow for the anterior segment; however, no reduction in blood flow was observed in the posterior segment of the eye after a topical dose of apraclonidine ophthalmic solution 0.5%. Ocular blood flow studies have not been conducted in humans.

INDICATIONS AND USAGE

Apraclonidine ophthalmic solution 0.5% is indicated for short-term adjunctive therapy, in patients on maximally tolerated medical therapy, who require additional IOP reduction. Patients on maximally tolerated medical therapy, who are treated with apraclonidine ophthalmic solution 0.5% to delay surgery, should have frequent follow-up examinations and treatment should be discontinued if the IOP rises significantly.

The addition of apraclonidine ophthalmic solution 0.5% to patients already using two aqueous suppressing drugs (i.e., beta-blocker plus carbonic anhydrase inhibitor) as part of their maximally tolerated medical therapy may not provide additional benefit. This is because apraclonidine ophthalmic solution 0.5% is an aqueous suppressing drug and the addition of a third aqueous suppressant may not significantly reduce IOP.

The IOP lowering efficacy of apraclonidine ophthalmic solution 0.5% diminishes over time in some patients. This loss of effect, or tachyphylaxis, appears to be an individual occurrence with a variable time of onset and should be closely monitored. The benefit for most patients is less than one month.

CONTRAINDICATIONS

Apraclonidine ophthalmic solution 0.5% is contraindicated in patients with hypersensitivity to apraclonidine or any other component of this medication, as well as systemic clonidine. It is also contraindicated in patients receiving monoamine oxidase (MAO) inhibitors.

WARNINGS

Not for injection or oral ingestion. FOR EYE USE ONLY.

PRECAUTIONS

General

Glaucoma patients on maximally tolerated medical therapy who are treated with apraclonidine ophthalmic solution 0.5% to delay surgery should have their visual fields monitored periodically.

Although the topical use of apraclonidine ophthalmic solution 0.5% has not been studied in renal failure patients, structurally related clonidine undergoes a significant increase in half-life in patients with severe renal impairment. Close monitoring of cardiovascular parameters in patients with impaired renal function is advised if they are candidates for topical apraclonidine therapy. Close monitoring of cardiovascular parameters in patients with impaired liver function is also advised as the systemic dosage form of clonidine is partly metabolized in the liver.

While the topical administration of apraclonidine ophthalmic solution 0.5% had minimal effect on heart rate or blood pressure in clinical studies evaluating glaucoma patients, the preclinical pharmacology profile of this drug suggests that caution should be observed in treating patients with severe, uncontrolled cardiovascular disease, including hypertension. The possibility of a vasovagal attack should be considered and caution should be exercised in patients with a history of such episodes.

Apraclonidine ophthalmic solution 0.5% should be used with caution in patients with coronary insufficiency, recent myocardial infarction, cerebrovascular disease, chronic renal failure, Raynaud’s disease, or thromboangiitis obliterans. Caution and monitoring of depressed patients are advised since apraclonidine has been infrequently associated with depression.

Apraclonidine can cause dizziness and somnolence. Patients who engage in hazardous activities requiring mental alertness should be warned of the potential for a decrease in mental alertness while using apraclonidine.

Topical ocular administration of two drops of 0.5%, 1.0%, and 1.5% apraclonidine ophthalmic solution to New Zealand albino rabbits three times daily for one month resulted in sporadic and transient instances of minimal corneal edema in the 1.5% group only; no histopathological changes were noted in those eyes.

Use of apraclonidine ophthalmic solution 0.5% can lead to an allergic-like reaction characterized wholly or in part by the symptoms of hyperemia, pruritus, discomfort, tearing, foreign body sensation, and edema of the lids and conjunctiva. If ocular allergic-like symptoms occur, apraclonidine ophthalmic solution 0.5% therapy should be discontinued.

Information for Patients

Do not touch dropper tip to any surface as this may contaminate the contents.

The preservative in apraclonidine ophthalmic solution 0.5%, benzalkonium chloride, may be absorbed by soft contact lenses. Contact lenses should be removed during instillation of apraclonidine ophthalmic solution 0.5% but may be reinserted 15 minutes after instillation.

Drug Interactions

Apraclonidine should not be used in patients receiving MAO inhibitors (see CONTRAINDICATIONS). Although no specific drug interactions with topical glaucoma drugs or systemic medications were identified in clinical studies of apraclonidine ophthalmic solution 0.5%, the possibility of an additive or potentiating effect with CNS depressants (alcohol, barbiturates, opiates, sedatives, anesthetics) should be considered. Tricyclic antidepressants have been reported to blunt the hypotensive effect of systemic clonidine. It is not known whether the concurrent use of these agents with apraclonidine can lead to a reduction in IOP lowering effect. No data on the level of circulating catecholamines after apraclonidine withdrawal are available. Caution, however, is advised in patients taking tricyclic antidepressants which can affect the metabolism and uptake of circulating amines.

An additive hypotensive effect has been reported with the combination of systemic clonidine and neuroleptic therapy. Systemic clonidine may inhibit the production of catecholamines in response to insulin-induced hypoglycemia and mask the signs and symptoms of hypoglycemia.

Since apraclonidine may reduce pulse and blood pressure, caution in using drugs such as beta-blockers (ophthalmic and systemic), antihypertensives, and cardiac glycosides is advised. Patients using cardiovascular drugs concurrently with apraclonidine ophthalmic solution 0.5% should have pulse and blood pressures frequently monitored. Caution should be exercised with simultaneous use of clonidine and other similar pharmacologic agents.

Carcinogenesis, Mutagenesis, Impairment of Fertility

No significant change in tumor incidence or type was observed following two years of oral administration of apraclonidine HCl to rats and mice at dosages of 1.0 and 0.6 mg/kg, up to 20 and 12 times, respectively, the maximum dose recommended for human topical ocular use.

Apraclonidine HCl was not mutagenic in a series of in vitro mutagenicity tests, including the Ames test, a mouse lymphoma forward mutation assay, a chromosome aberration assay in cultured Chinese hamster ovary (CHO) cells, a sister chromatid exchange assay in CHO cells, and a cell transformation assay. An in vivo mouse micronucleus assay conducted with apraclonidine HCl also provided no evidence of mutagenicity.

Reproduction and fertility studies in rats showed no adverse effect on male or female fertility at a dose of 0.5 mg/kg (5 to 10 times the maximum recommended human dose).

Pregnancy

Apraclonidine HCl has been shown to have an embryocidal effect in rabbits when given in an oral dose of 3.0 mg/kg (60 times the maximum recommended human dose). Dose related maternal toxicity was observed in pregnant rats at 0.3 mg/kg (6 times the maximum recommended human dose). There are no adequate and well controlled studies in pregnant women. Apraclonidine ophthalmic solution 0.5% should be used during pregnancy only if the potential benefit justifies the potential risk to the fetus.

Nursing Mothers

It is not known whether this drug is excreted in human milk. Because many drugs are excreted in human milk, caution should be exercised when apraclonidine ophthalmic solution 0.5% is administered to a nursing woman.

Pediatric Use

Safety and effectiveness in pediatric patients have not been established.

Geriatric Use

No overall differences in safety or effectiveness have been observed between elderly and younger patients.

ADVERSE REACTIONS

In clinical studies the overall discontinuation rate related to apraclonidine ophthalmic solution 0.5% was 15%. The most commonly reported events leading to discontinuation included (in decreasing order of frequency) hyperemia, pruritus, tearing, discomfort, lid edema, dry mouth, and foreign body sensation.

The following adverse reactions (incidences) were reported in clinical studies of apraclonidine ophthalmic solution 0.5% as being possibly, probably, or definitely related to therapy:

Ocular

The following adverse reactions were reported in 5% to 15% of the patients: discomfort, hyperemia, and pruritus.

The following adverse reactions were reported in 1% to 5% of the patients: blanching, blurred vision, conjunctivitis, discharge, dry eye, foreign body sensation, lid edema, and tearing.

The following adverse reactions were reported in less than 1% of the patients: abnormal vision, blepharitis, blepharoconjunctivitis, conjunctival edema, conjunctival follicles, corneal erosion, corneal infiltrate, corneal staining, edema, irritation, keratitis, keratopathy, lid disorder, lid erythema, lid margin crusting, lid retraction, lid scales, pain, and photophobia.

Nonocular

Dry mouth occurred in approximately 10% of the patients.

The following adverse reactions were reported in less than 3% of the patients: abnormal coordination, asthenia, arrhythmia, asthma, chest pain, constipation, contact dermatitis, depression, dermatitis, dizziness, dry nose, dyspnea, facial edema, headache, insomnia, malaise, myalgia, nausea, nervousness, paresthesia, parosmia, peripheral edema, pharyngitis, rhinitis, somnolence, and taste perversion.

Clinical Practice

The following events have been identified during postmarketing use of apraclonidine ophthalmic solution 0.5% in clinical practice. Because they are reported voluntarily from a population of unknown size, estimates of frequency cannot be made. The events, which have been chosen for inclusion due to either their seriousness, frequency of reporting, possible causal connection to apraclonidine ophthalmic solution 0.5%, or a combination of these factors, include bradycardia and hypersensitivity.

OVERDOSAGE

Ingestion of apraclonidine ophthalmic solution 0.5% has been reported to cause bradycardia, drowsiness, and hypothermia.

Accidental or intentional ingestion of oral clonidine has been reported to cause apnea, arrhythmias, asthenia, bradycardia, conduction defects, diminished or absent reflexes, dryness of the mouth, hypotension, hypothermia, hypoventilation, irritability, lethargy, miosis, pallor, respiratory depression, sedation or coma, seizure, somnolence, transient hypertension, and vomiting.

Treatment of an oral overdose includes supportive and symptomatic therapy; a patent airway should be maintained. Hemodialysis is of limited value since a maximum of 5% of circulating drug is removed.

DOSAGE AND ADMINISTRATION

One to two drops of apraclonidine ophthalmic solution 0.5% should be instilled in the affected eye(s) three times daily. Since apraclonidine ophthalmic solution 0.5% will be used with other ocular glaucoma therapies, an approximate 5 minute interval between instillation of each medication should be practiced to prevent washout of the previous dose. NOT FOR INJECTION INTO THE EYE. NOT FOR ORAL INGESTION.

HOW SUPPLIED

Apraclonidine ophthalmic solution 0.5% as base in a sterile, isotonic, aqueous solution containing apraclonidine hydrochloride.

Supplied in plastic ophthalmic dispenser as follows:

5 mL NDC 61314-665-05

10 mL NDC 61314-665-10

Storage: Store between 2° to 25°C (36° to 77°F). Protect from freezing and light.

To report SUSPECTED ADVERSE REACTIONS, contact Sandoz Inc., at 1-800-525-8747 or FDA at 1-800-FDA-1088 or www.fda.gov/medwatch.

Manufactured by
Alcon Laboratories, Inc.
Fort Worth, Texas 76134 for
Sandoz Inc., Princeton, NJ 08540

Rev. 01/2024

PRINCIPLE DISPLAY PANEL - 5mL Carton

NDC 61314-665-05
Apraclonidine

Ophthalmic

Solution

0.5% as base
0.5%
Rx Only

FOR EYE USE ONLY
STERILE
5 mL
SANDOZ

PRINCIPLE DISPLAY PANEL - 10mL Carton

NDC 61314-665-10
Apraclonidine

Ophthalmic

Solution

0.5% as base
0.5%
Rx Only

FOR EYE USE ONLY
STERILE
10 mL

SANDOZ

SANDOZ